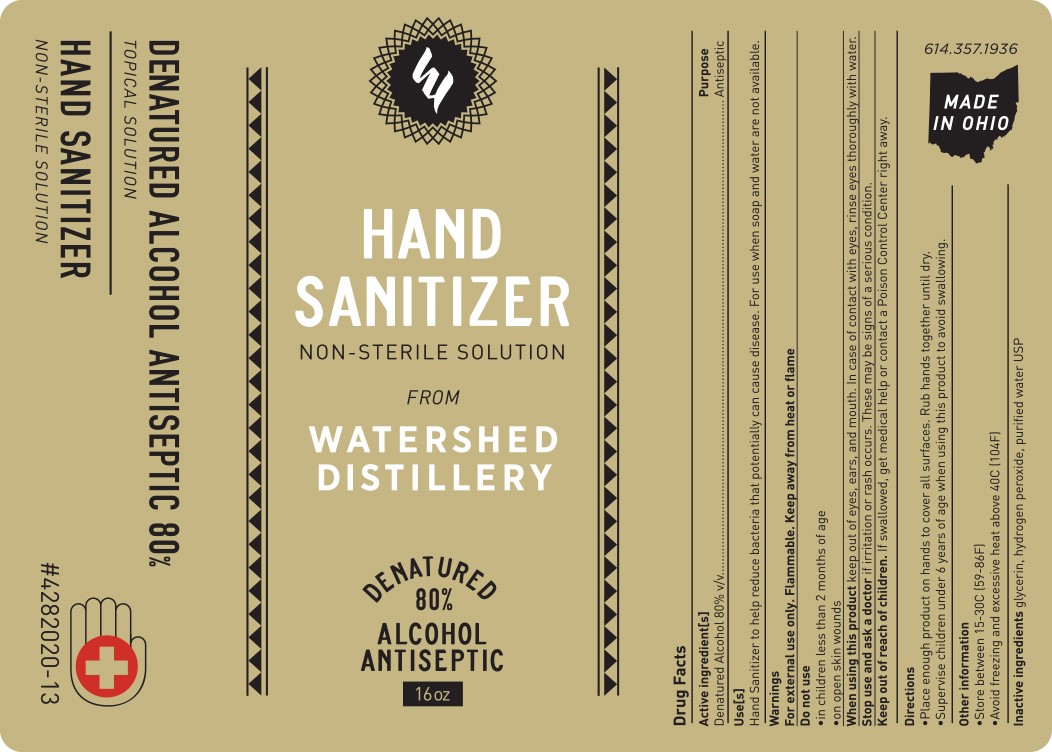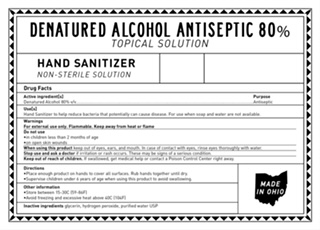 DRUG LABEL: HAND SANITIZER
NDC: 74008-0001 | Form: LIQUID
Manufacturer: Watershed Distillery LLC
Category: otc | Type: HUMAN OTC DRUG LABEL
Date: 20200512

ACTIVE INGREDIENTS: ALCOHOL 378.4 mL/473 mL
INACTIVE INGREDIENTS: GLYCEROL FORMAL 6.86 mL/473 mL; WATER 87.15 mL/473 mL; HYDROGEN PEROXIDE 0.59 mL/473 mL

ACTIVE INGREDIENT

Alcohol 80%

Do not use:
In children less than 2 months of age
On open skin wounds

Keep out of reach of children. If swallowed, get medical help or contact a Poison Control Center right away.

PURPOSE

Use(s)
Hand sanitizer to help reduce bacteria that potentially can cause disease. For use when soap and water are not available.

Stop use and ask a doctor if irritation or rash occurs. These may be signs of a serious condition.

When using this product keep out of eyes, ears, and mouth. In case of contact with eyes, rinse eyes thoroughly with water

Other information:
Store between 15-30C (59-86F)
Avoid freezing and excessive heat above 40C (104F)

Warnings:
For external use only. Flammable. Keep away from heat or flame.

Directions:
Place enough product on hands to cover all surfaces. Rub hands together until dry.
Supervise children under 6 years of age when using this product to avoid swallowing.

Inactive ingredients glycerin, hydrogen peroxide, purified water USP

Directions
Place enough product on hands to cover all surfaces. Rub hands together until dry.
Supervise children under 6 years of age when using this product to avoid swallowing.

WARNINGS

For external use only. Flammable. Keep away from heat or flame.

For external use only. Flammable. Keep away from heat or flame.
When using this product keep out of eyes, ears, and mouth. In case of contact with eyes, rinse eyes thoroughly with water
Stop use and ask a doctor if irritation or rash occurs. These may be signs of a serious condition. Keep out of reach of children. If swallowed, get medical help or contact a Poison Control Center right away.

INDICATIONS AND USAGE

Usage: Hand sanitizer to help reduce bacteria that potentially can cause disease. For use when soap and water are not available.
Directions
Place enough product on hands to cover all surfaces. Rub hands together until dry.
Supervise children under 6 years of age when using this product to avoid.

PACKAGE LABEL

Hand Sanitizer
Non-Sterile Solution
Denatured Alcohol Antiseptic 80%
Topical Solution
______mL ________ BATCH